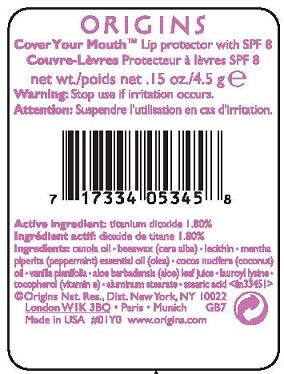 DRUG LABEL: COVER YOUR MOUTH
NDC: 59427-575 | Form: LIPSTICK
Manufacturer: ORIGINS NATURAL RESOURCES INC.
Category: otc | Type: HUMAN OTC DRUG LABEL
Date: 20110727

ACTIVE INGREDIENTS: TITANIUM DIOXIDE 1.8 g/100 g
INACTIVE INGREDIENTS: CANOLA OIL; WHITE WAX; LECITHIN, SOYBEAN; PEPPERMINT OIL; COCONUT OIL; VANILLA; LAUROYL LYSINE; ALPHA-TOCOPHEROL; ALUMINUM STEARATE; STEARIC ACID

active ingredient: titanium dioxide 1.80%

INACTIVE INGREDIENT

inactive ingredients: canola oil [] beeswax (cera alba) [] lecithin [] mentha piperita (peppermint) essential oil (olea) [] cocos nucifera (coconut) oil [] vanilla planifolia [] aloe barbadensis (aloe) leaf juice [] lauroyl lysine [] tocopherol (vitamin e) [] aluminum stearate [] stearic acid

WARNINGS

warning: stop use if signs of irritation appear and check with doctor.

PACKAGE LABEL

PRINCIPAL DISPLAY PANEL
ORIGINS
COVER YOUR MOUTH
LIP PROTECTOR
WITH SPF 8
NT WT 0.15 OZ./ 4.5 G
origins natural resources inc.
new york, ny 10022